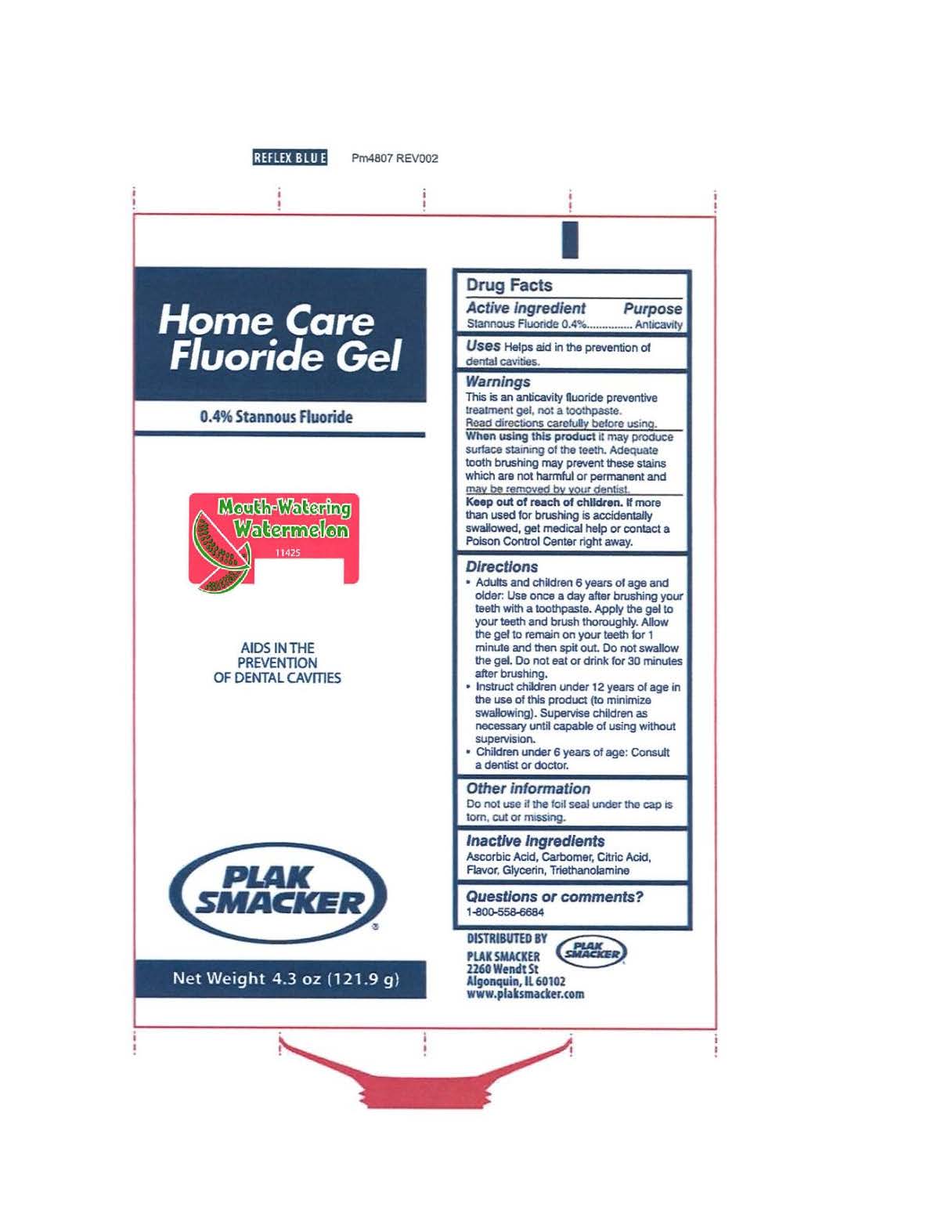 DRUG LABEL: Plak Smacker
NDC: 55346-0431 | Form: GEL
Manufacturer: Dental Technologies, Inc.
Category: otc | Type: HUMAN OTC DRUG LABEL
Date: 20151001

ACTIVE INGREDIENTS: STANNOUS FLUORIDE 0.969 mg/1 g
INACTIVE INGREDIENTS: ASCORBIC ACID; CARBOMER 934; ANHYDROUS CITRIC ACID; GLYCERIN; TROLAMINE

Drug Facts

Active Ingredient

Stannous Fluoride 0.4%

Purpose

Anticavity

Uses

Helps aid in the prevention of dental cavities.

Warnings:

This is an anticavity fluoride preventive treatment gel, not a toothpaste.

Read directions carefully before using.

When using this product it may produce surface staining of the teeth. Adequate tooth brushing may prevent these stains which are not harmful to permanent and may be removed by your dentist.

Keep out of reach of children.

If more than used for brushing is accidentally swallowed, get medical help or contact a Poison Control Center right away.

Directions:

- Adults and children 6 years of age and older: Use once a day after brushing your teeth with a toothpaste. Apply the gel to your teeth and brush thoroughly. Allow the gel to remain on your teeth for 1 minute and then spit out. Do not swallow the gel. Do not eat or drink for 30 minutes after brushing.
- Instruct children under 12 years of age in the use of this product (to minimize swallowing). Supervise children as necessary until capable of using without supervision.
- Children under 6 years of age: Consult a dentist or doctor.

Other Information

Do not use if the foil seal under the cap is torn, cut or missing.

Inactive Ingredients:

Ascorbic Acid, Carbomer, Citric Acid, Flavor, Glycerin, Triethanolamine

Questions or comments?

1-800-558-6684

Principal Display Panel

HOME CARE

FLUORIDE GEL

0.4% STANNOUS FLUORIDE

Mouth-Watering Watermelon

11425

AIDS IN THE

PREVENTION

OF DENTAL CAVITIES

PLAK SMACKER

NET WEIGHT - 4.3 oz. (121.9g)